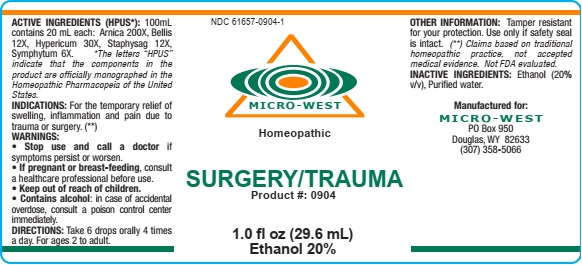 DRUG LABEL: Surgery/Trauma
NDC: 61657-0904 | Form: LIQUID
Manufacturer: White Manufacturing Inc. DBA Micro-West
Category: homeopathic | Type: HUMAN OTC DRUG LABEL
Date: 20210121

ACTIVE INGREDIENTS: ST. JOHN'S WORT 30 [hp_X]/30 mL; ARNICA MONTANA FLOWER 200 [hp_X]/30 mL; COMFREY ROOT 6 [hp_X]/30 mL; BELLIS PERENNIS 12 [hp_X]/30 mL; DELPHINIUM STAPHISAGRIA SEED 12 [hp_X]/30 mL
INACTIVE INGREDIENTS: ALCOHOL

DRUG FACTS

ACTIVE INGREDIENTS

Arnica 200X

Bellis 12X

Hypericum 30X

Staphysagria 12X

Symphytum 6X

PURPOSE

FOR THE TEMPORARY RELIEF OF SWELLING, INFLAMMATION AND PAIN DUE TO TRAUMA OR SURGERY

KEEP OUT OF REACH OF CHILDREN

INDICATIONS

FOR THE TEMPORARY RELIEF OF SWELLING, INFLAMMATION AND PAIN DUE TO TRAUMA OR SURGERY

WARNINGS

WARNING: Stop use and call a doctor if symptoms persist or worsen .Contains alcohol: in case of accidental overdose, consult a poison control center immediately

PREGNANCY

If pregnant or breast-feeding, consult a healthcare professional before use.

DIRECTIONS

DIRECTIONS: Take 6 drops 4 times a day. For ages 2 to adult

INACTIVE INGREDIENTS

Alcohol (20% v/v)

Purified water

MANUFACTURE

MANUFACTURED FOR

MICRO-WEST

P.O. Box 950

DOUGLAS, WY 82633

1-307-358-5066

LABEL

NDC 61657-0904-1

MICRO-WEST

Homeopathic

SURGERY/TRAUMA

Product #: 0904

1.0 fl oz (29.6 mL)

Ethanol 20%